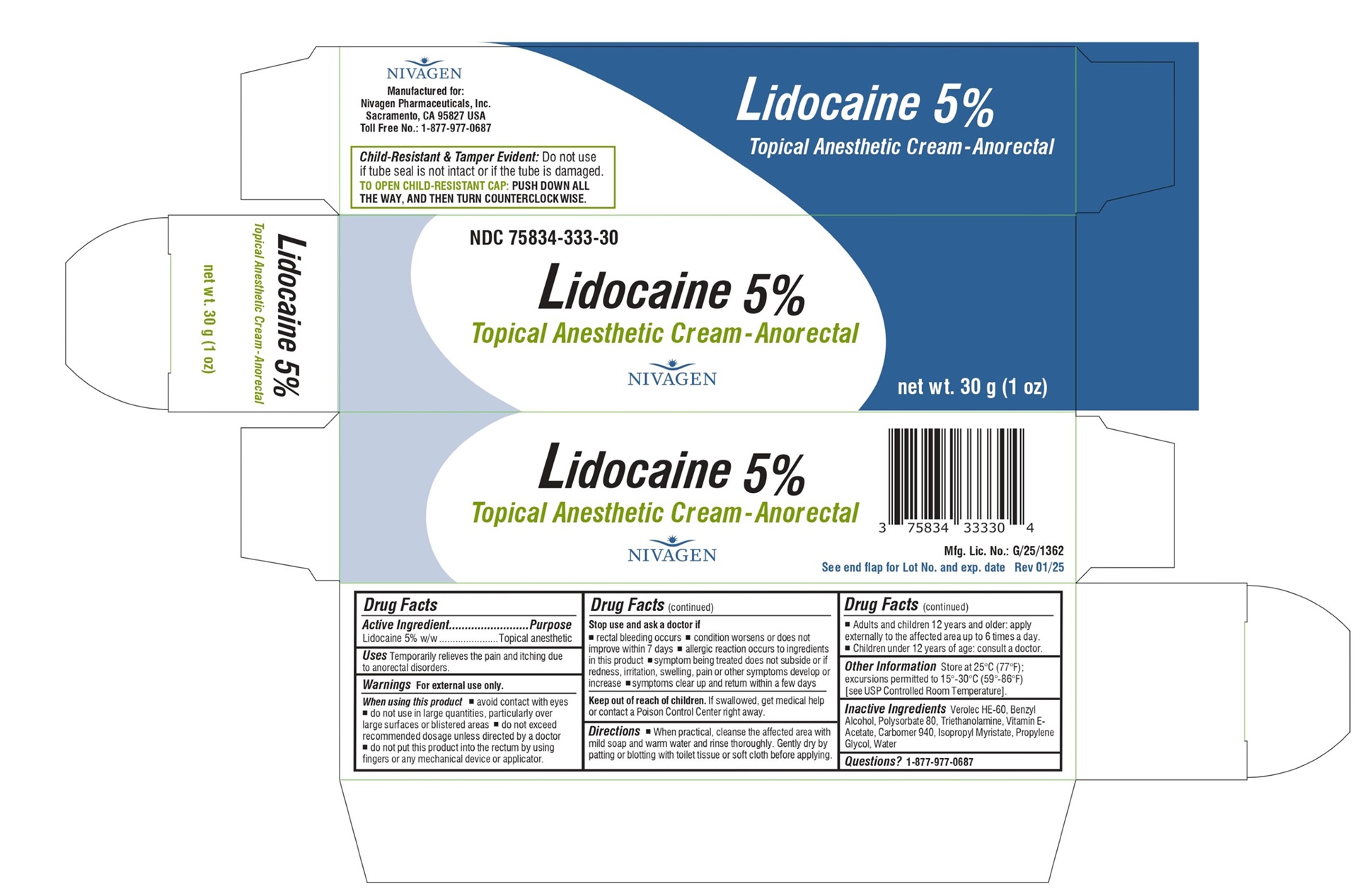 DRUG LABEL: lidocaine
NDC: 75834-333 | Form: CREAM
Manufacturer: Nivagen Pharmaceuticals, Inc.
Category: otc | Type: Human OTC Drug Label
Date: 20250123

ACTIVE INGREDIENTS: LIDOCAINE 50 mg/1 g
INACTIVE INGREDIENTS: HYDROGENATED SOYBEAN LECITHIN; BENZYL ALCOHOL; POLYSORBATE 80; TRIETHANOLAMINE; .ALPHA.-TOCOPHEROL ACETATE; CARBOMER 940; ISOPROPYL MYRISTATE; PROPYLENE GLYCOL; WATER

Lidocaine 5%
Drug Facts

Active Ingredient

Lidocaine 5% w/w

Purpose

Topical anesthetic

Uses

Temporarily relieves the pain and itching due to anorectal disorders.

Warnings

For external use only.

When using this product

- avoid contact with eyes
- do not use in large quantities, particularly over large surfaces or blistered areas
- do not exceed recommended dosage unless directed by a doctor
- do not put this product into the rectum by using fingers or any mechanical device or applicator

Stop use and ask a doctor if

- rectal bleeding occurs
- condition worsens or does not improve within 7 days
- allergic reaction occurs to ingredients in this product
- symptom being treated does not subside or if redness, irritation, swelling, pain or other symptoms develop or increase
- symptoms clear up and return within a few days

Keep out of reach of children.

If swallowed, get medical help or contact a Poison Control Center right away.

Directions

- When practical, cleanse the affected area with mild soap and warm water and rinse thoroughly. Gently dry by patting or blotting with toilet tissue or soft cloth before applying.
- Adults and children 12 years and older: apply externally to the affected area up to 6 times a day.
- Children under 12 years of age: consult a doctor.

Other Information

Store at 25°C (77°F); excursions permitted to 15°-30°C (59°-86°F) [see USP Controlled Room Temperature].

Inactive Ingredients

Verolec HE 60, Benzyl Alcohol, Polysorbate 80, Triethanolamine, Vitamin E- Acetate, Carbomer 940, Isopropyl Myristate, Propylene Glycol, Water

Questions?

1-877-977-0687

PRINCIPAL DISPLAY PANEL - 30 g Tube Carton

NDC 75834-333-30
Lidocaine 5%
Topical Anesthetic Cream-Anorectal
NIVAGEN
net wt. 30 g (1 oz)